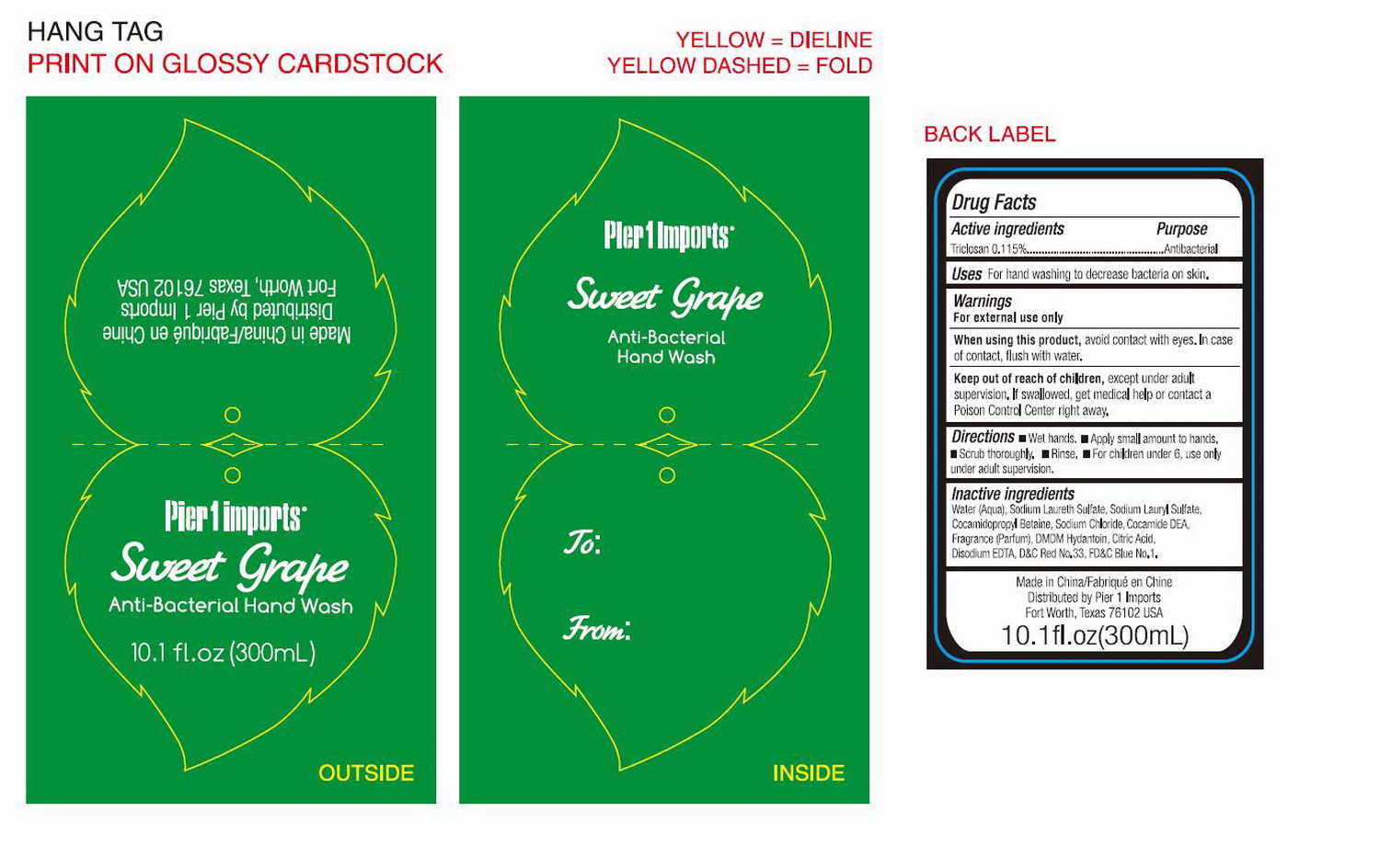 DRUG LABEL: Pier 1 Imports Sweet Grape Anti-bacterial Hand Wash
NDC: 49981-017 | Form: LIQUID
Manufacturer: Xiamen Anna Global Co., Ltd
Category: otc | Type: HUMAN OTC DRUG LABEL
Date: 20091203

ACTIVE INGREDIENTS: TRICLOSAN 0.115 g/100 g
INACTIVE INGREDIENTS: WATER 81.195465 g/100 g; SODIUM LAURETH SULFATE 10 g/100 g; SODIUM LAURYL SULFATE 2.5 g/100 g; COCAMIDOPROPYL BETAINE 2.5 g/100 g; SODIUM CHLORIDE 1.85 g/100 g; 1,3-DIMETHYLOL-5,5-DIMETHYL-HYDANTOIN 0.5 g/100 g; ANHYDROUS CITRIC ACID 0.009 g/100 g; EDETATE DISODIUM 0.03 g/100 g; D&C RED NO. 33 0.00016 g/100 g; FD&C BLUE NO. 1 0.000375 g/100 g

Drug Fact

Active ingredients Purpose

Triclosan 0.115% Antibacterial

DESCRIPTION

Uses For hand washing to decrease bacteria on skin

Warnings

For external use only

When using this product，avoid contact with eyes. In case of contact, flush with water

Keep out of reach of children, except under adult supervision. If swallowed, get medical help or contact a Poison Control Center right away

WHEN USING

Directions Wet hands. Apply small amount to hands. Scrub thoroughly. Rinse. For children under 6, use only under adult supervision

Inactive ingredients

Water (Aqua), Sodium Laureth Sulfate, Sodium Lauryl Sulfate, Cocamidopropyl Betaine, Sodium Chloride, Cocamide DEA, Fragrance (Parfum), DMDM Hydantoin, Citric acid, Disodium EDTA, D and C Red No. 33, FD and C Blue No. 1

label